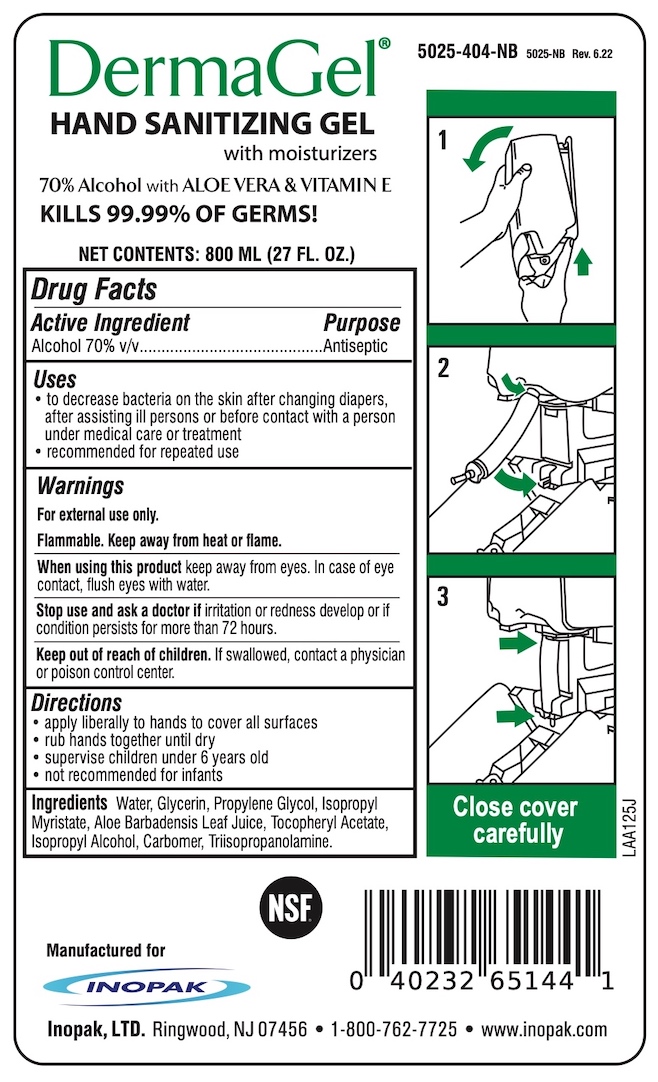 DRUG LABEL: DermaGel
NDC: 58575-231 | Form: GEL
Manufacturer: Inopak. Ltd
Category: otc | Type: HUMAN OTC DRUG LABEL
Date: 20220629

ACTIVE INGREDIENTS: ALCOHOL 70 mL/100 mL
INACTIVE INGREDIENTS: ALOE VERA LEAF; GLYCERIN; CARBOMER INTERPOLYMER TYPE B (ALLYL PENTAERYTHRITOL CROSSLINKED); WATER; TRIISOPROPANOLAMINE; .ALPHA.-TOCOPHEROL ACETATE; ISOPROPYL MYRISTATE; ISOPROPYL ALCOHOL; PROPYLENE GLYCOL

DermaGel Clear Hand Sanitizing Gel

Drug Facts

Active Ingredient

Alcohol 70% v/v

Purpose

Antiseptic

Uses

- to decrease bacteria on the skin after changing diapers, after assisting ill persons or before contact with a person under medical care or treatment
- recommended for repeated use.

Warnings

For external use only

Flammable. Keep away from heat or flame.

When using this product keep away from eyes. In case of eye contact, flush with water.

Stop use and ask a doctor if irritation or redness develop or if condition persists for more than 72 hours.

Keep out of reach of children. If swallowed, contact a physician or poison control center.

Directions

- apply liberally to hands to cover all surfaces
- rub hands together until dry
- supervise children under 6 years old
- not recommended for infants

INACTIVE INGREDIENT

Ingredients Water, Glycerin, Propylene Glycol, Isopropy Myristate, Aloe Barbedensis Leaf Juice, Tocopheryl Acetate, Isopropyl Alcohol, Carbomer, Triisopropanolamine

Manufactured for Inopak, LTD., Ringwood, NJ 07456

1-800-762-7725 • www.inopak.com

PACKAGE LABEL

DermaGel®

HAND SANITIZING GEL with moisturizers

70% Alcohol with ALOE VERA & VITAMIN E

KILLS 99.99% OF GERMS!

NET CONTENTS: 800 ML (27 FL. OZ.)